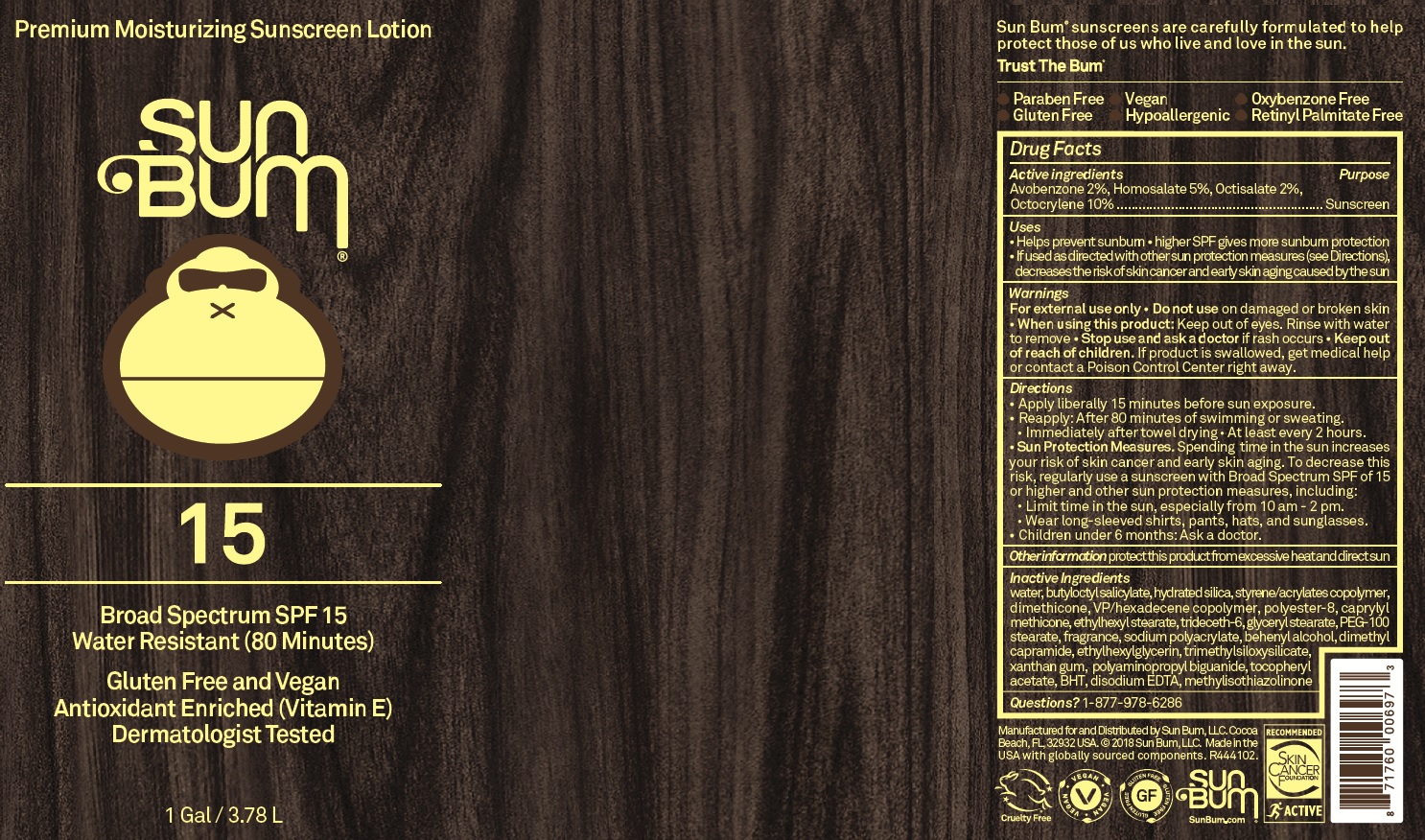 DRUG LABEL: SUN BUM SPF 15 PREMIUM MOISTURIZING SUNSCREEN
NDC: 69039-212 | Form: LOTION
Manufacturer: Sun Bum, LLC.
Category: otc | Type: HUMAN OTC DRUG LABEL
Date: 20220228

ACTIVE INGREDIENTS: AVOBENZONE 20 mg/1 mL; HOMOSALATE 50 mg/1 mL; OCTISALATE 20 mg/1 mL; OCTOCRYLENE 100 mg/1 mL
INACTIVE INGREDIENTS: WATER; BUTYLOCTYL SALICYLATE; HYDRATED SILICA; STYRENE; DIMETHICONE; VINYLPYRROLIDONE/HEXADECENE COPOLYMER; CAPRYLYL TRISILOXANE; ETHYLHEXYL STEARATE; TRIDECETH-6; GLYCERYL MONOSTEARATE; POLYETHYLENE GLYCOL 4500; DOCOSANOL; DIMETHYL CAPRAMIDE; ETHYLHEXYLGLYCERIN; XANTHAN GUM; POLYAMINOPROPYL BIGUANIDE; .ALPHA.-TOCOPHEROL ACETATE; BUTYLATED HYDROXYTOLUENE; EDETATE DISODIUM ANHYDROUS; METHYLISOTHIAZOLINONE

SUN BUM SPF 15 PREMIUM MOISTURIZING SUNSCREEN

Active ingredients

Avobenzone 2%, Homosalate 5%, Octisalate 2%, Octocrylene 10%

Purpose

Sunscreen

Uses

• Helps prevent sunburn • higher SPF gives more sunburn protection • Ifusedasdirectedwithothersunprotectionmeasures(seeDirections), decreasestheriskofskincancerandearlyskinagingcausedbythesun

Warnings

For external use only

Do not use

- on damaged or broken skin

When using this product:

- Keep out of eyes. Rinse with water to remove

Stop use and ask a doctor

- if rash occurs

Keep out of reach of children.

- If product is swallowed, get medical help or contact a Poison Control Center right away.

Directions

• Apply liberally 15 minutes before sun exposure.
• Reapply: After 80 minutes of swimming or sweating.
• Immediately after towel drying • At least every 2 hours.
• Sun Protection Measures. Spending time in the sun increases your risk of skin cancer and early skin aging. To decrease this risk, regularly use a sunscreen with Broad Spectrum SPF of 15 or higher and other sun protection measures, including:
• Limit time in the sun, especially from 10 am - 2 pm.
• Wear long-sleeved shirts, pants, hats, and sunglasses.
• Children under 6 months: Ask a doctor.

Otherinformation

protectthis product from excessive heat and direct sun

Inactive Ingredients

water, butyloctylsalicylate, hydratedsilica, styrene/acrylatescopolymer, dimethicone, VP/hexadecene copolymer, polyester-8, caprylyl methicone, ethylhexyl stearate, trideceth-6, glyceryl stearate, PEG-100 stearate, fragrance, sodium polyacrylate, behenyl alcohol, dimethyl capramide, ethylhexylglycerin, trimethylsiloxysilicate, xanthan gum, polyaminopropyl biguanide, tocopheryl acetate, BHT, disodium EDTA, methylisothiazolinone

Questions?

1-877-978-6286